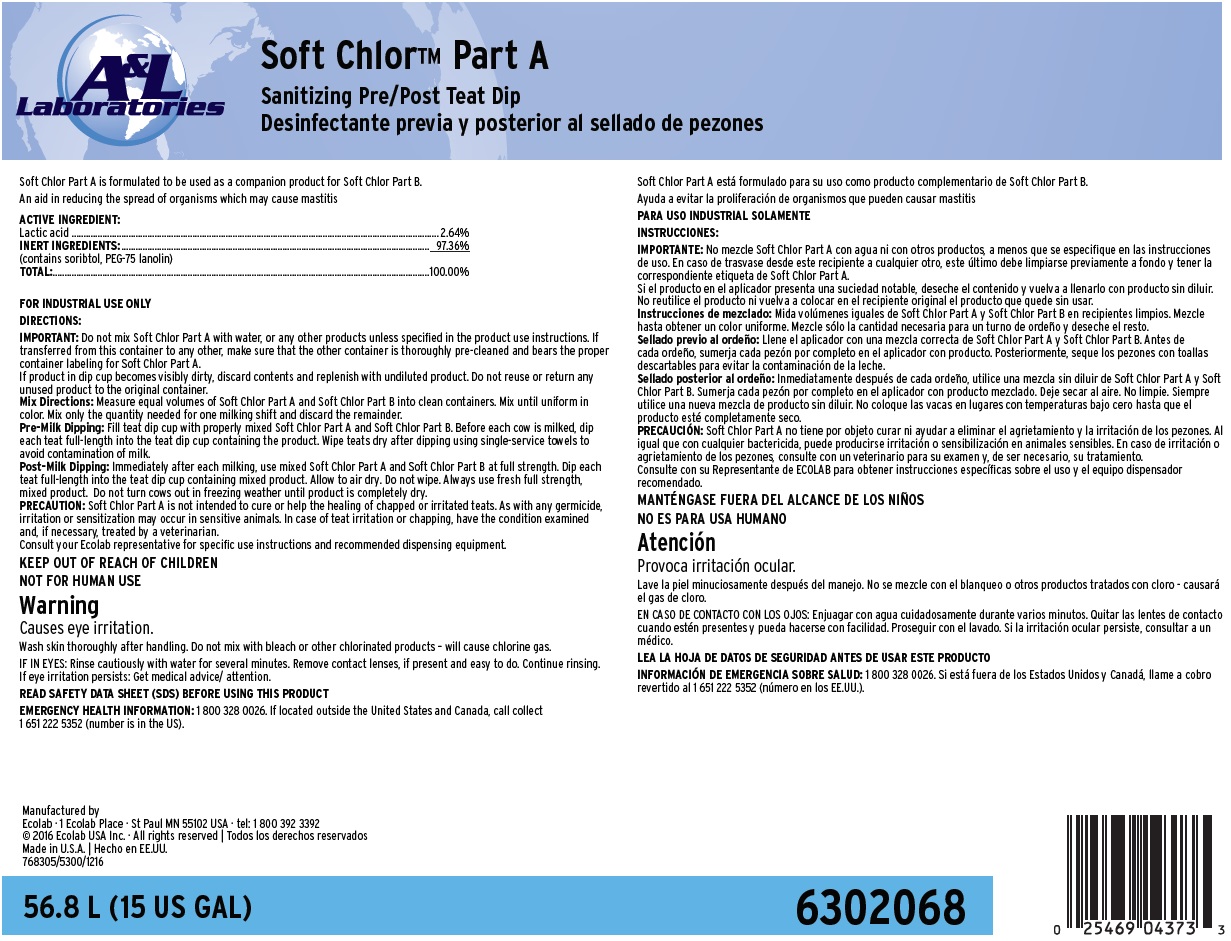 DRUG LABEL: Soft Chlor Part A
NDC: 47593-542 | Form: SOLUTION
Manufacturer: Ecolab Inc.
Category: animal | Type: OTC ANIMAL DRUG LABEL
Date: 20250926

ACTIVE INGREDIENTS: LACTIC ACID 26.4 mg/1 mL
INACTIVE INGREDIENTS: SORBITOL; PEG-75 LANOLIN; WATER

SAFE HANDLING WARNING

FOR INDUSTRIAL USE ONLY

KEEP OUT OF REACH OF CHILDREN

NOT FOR HUMAN USE

Warning

Causes eye irritation.

Wash skin thoroughly after handling. Do not mix with bleach or other chlorinated products – will cause chlorine gas.

DIRECTIONS:
IMPORTANT: Do not mix Soft Chlor Part A with water, or any other products unless specified in the product use instructions. If transferred from this container to any other, make sure that the other container is thoroughly pre-cleaned and bears the proper container labeling for Soft Chlor Part A.
If product in dip cup becomes visibly dirty, discard contents and replenish with undiluted product. Do not reuse or return any unused product to the original container.
Mix Directions: Measure equal volumes of Soft Chlor Part A and Soft Chlor Part B into clean containers. Mix until uniform in color. Mix only the quantity needed for one milking shift and discard the remainder.
Pre-Milk Dipping: Fill teat dip cup with properly mixed Soft Chlor Part A and Soft Chlor Part B. Before each cow is milked, dip each teat full-length into the teat dip cup containing the product. Wipe teats dry after dipping using single-service towels to avoid contamination of milk.
Post-Milk Dipping: Immediately after each milking, use mixed Soft Chlor Part A and Soft Chlor Part B at full strength. Dip each teat full-length into the teat dip cup containing mixed product. Allow to air dry. Do not wipe. Always use fresh full strength, mixed product. Do not turn cows out in freezing weather until product is completely dry.
PRECAUTION: Soft Chlor Part A is not intended to cure or help the healing of chapped or irritated teats. As with any germicide, irritation or sensitization may occur in sensitive animals. In case of teat irritation or chapping, have the condition examined and, if necessary, treated by a veterinarian.
Consult your Ecolab representative for specific use instructions and recommended dispensing equipment.

OTHER SAFETY INFORMATION

IF IN EYES: Rinse cautiously with water for several minutes. Remove contact lenses, if present and easy to do. Continue rinsing. If eye irritation persists: Get medical advice/ attention.
READ SAFETY DATA SHEET (SDS) BEFORE USING THIS PRODUCT
EMERGENCY HEALTH INFORMATION: 1 800 328 0026. If located outside the United States and Canada, call collect 1 651 222 5352 (number is in the US).

Representative Label and Principal Display Panel

A&L Laboratories

Soft Chlor™ Part A

Sanitizing Pre/Post Teat Dip

Soft Chlor Part A is formulated to be used as a companion product for Soft Chlor Part B.

An aid in reducing the spread of organisms which may cause mastitis

ACTIVE INGREDIENT:
Lactic acid .................................................................................................... 2.64%
SKIN CONDITIONING SYSTEM:
(contains sorbitol, PEG-75 lanolin).................................................................. 10.00%
INERT INGREDIENTS:................................................................................. 87.36%
TOTAL:......................................................................................................100.00%

Manufactured by
Ecolab · 1 Ecolab Place · St Paul MN 55102 USA · tel: 1 800 392 3392
© 2016 Ecolab USA Inc. · All rights reserved
Made in U.S.A.
768305/5300/1216

56.8L (15 US GAL) 6302068